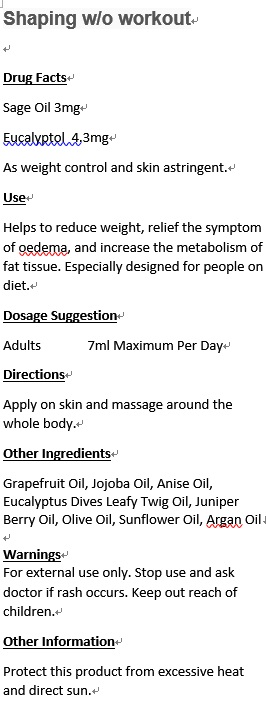 DRUG LABEL: Shaping without workout
NDC: 70470-8001 | Form: OIL
Manufacturer: PHYTOPIA CO., LTD.
Category: otc | Type: HUMAN OTC DRUG LABEL
Date: 20160505

ACTIVE INGREDIENTS: EUCALYPTOL 4.3 mg/50 mL; SAGE OIL 3 mg/50 mL
INACTIVE INGREDIENTS: EUCALYPTUS DIVES LEAFY TWIG OIL; ANISE OIL; GRAPEFRUIT OIL; JUNIPER BERRY OIL; JOJOBA OIL; OLIVE OIL; SUNFLOWER OIL; ARGAN OIL

Drug Facts

Sage Oil 3mg

Eucalyptol 4.3mg

As Weight Control And Skin Astringent.

Use

Helps to reduce weight, relief the symptom of oedema, and increase the metabolism of fat tissue. Especially designed for people on diet.

Dosage Suggestion

Adults 7ml Maximum Per Day

Directions

Apply on skin and massage around the whole body.

INACTIVE INGREDIENT

Other Ingredients

Grapefruit Oil, Jojoba Oil, Anise Oil, Eucalyptus Dives Leafy Twig Oil, Juniper Berry Oil, Olive Oil, Sunflower Oil, Argan Oil

Warnings

For external use only. Stop use and ask doctor if rash occurs. Keep out of reach of children.

Warnings

For external use only. Stop use and ask doctor if rash occurs. Keep out of reach of children.

Other Information

Protect this product from excessive heat and direct sun.

PACKAGE LABEL

Shaping w/o Workout